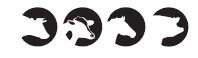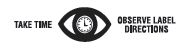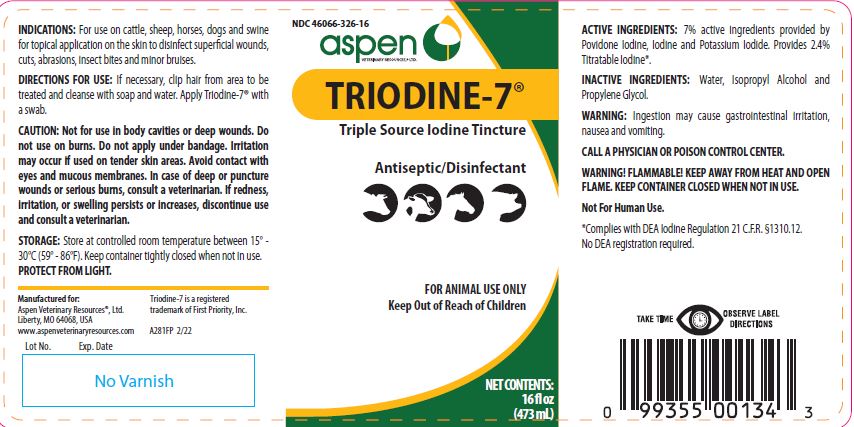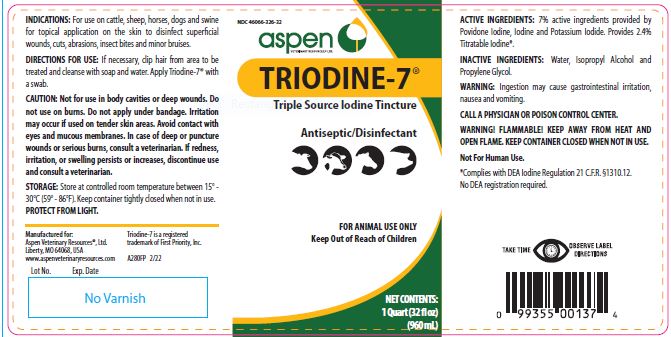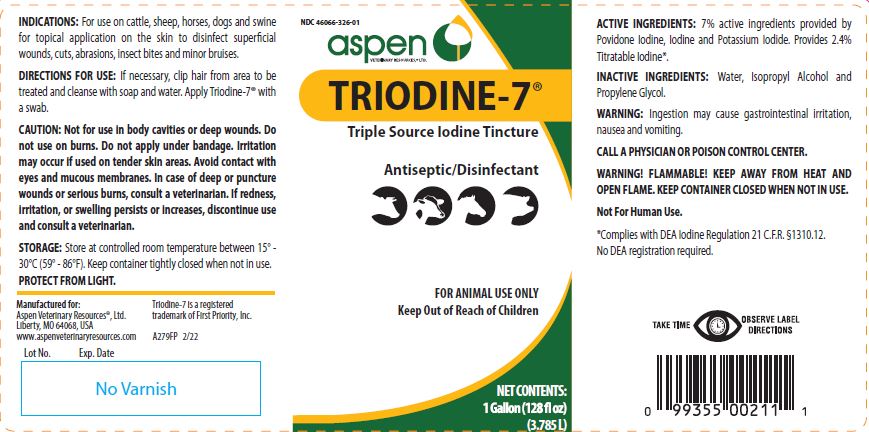 DRUG LABEL: Triodine
NDC: 46066-326 | Form: SOLUTION
Manufacturer: Aspen Veterinary
Category: animal | Type: OTC ANIMAL DRUG LABEL
Date: 20230807

ACTIVE INGREDIENTS: IODINE 2.1 mg/1 mL; POVIDONE-IODINE 3.0 mg/1 mL; POTASSIUM IODIDE 2.0 mg/1 mL

TRIODINE-7®

PURPOSE

Triple Source Iodine Tincture

Antiseptic/Disinfectant

KEEP OUT OF REACH OF CHILDREN

FOR ANIMAL USE ONLY
Keep Out of Reach of Children

NET CONTENTS:

16 fl oz (473 mL)

1 Quart (32 fl oz) (960 mL)

1 Gallon (128 fl oz) (3.785 L)

INDICATIONS:

For use on cattle, sheep, horses, dogs and swine for topical application on the skin to disinfect superficial wounds, cuts, abrasions, insect bites and minor bruises.

DIRECTIONS FOR USE:

If necessary, clip hair from area to be treated and cleanse with soap and water. Apply Triodine-7® with a swab.

CAUTION:

Not for use in body cavities or deep wounds. Do not use on burns. Do not apply under bandage. Irritation may occur if used on tender skin areas. Avoid contact with eyes and mucous membranes. In case of deep or puncture wounds or serious burns, consult a veterinarian. If redness, irritation, or swelling persists or increases, discontinue use and consult a veterinarian.

STORAGE:

Store at controlled room temperature between 15° - 30°C (59° - 86°F). Keep container tightly closed when not in use.
PROTECT FROM LIGHT.

ACTIVE INGREDIENTS:

7% active ingredients provided by Povidone Iodine, Iodine and Potassium Iodide. Provides 2.4% Titratable Iodine*.

INACTIVE INGREDIENTS:

Water, Isopropyl Alcohol and Propylene Glycol.

WARNING:

Ingestion may cause gastrointestinal irritation, nausea and vomiting.

CALL A PHYSICIAN OR POISON CONTROL CENTER. WARNING! FLAMMABLE! KEEP AWAY FROM HEAT AND OPEN FLAME. KEEP CONTAINER CLOSED WHEN NOT IN USE.
Not For Human Use.

*Complies with DEA Iodine Regulation 21 C.F.R. §1310.12. No DEA registration required.

INFORMATION FOR OWNERS/CAREGIVERS

Triodine-7 is a registered trademark of First Priority, Inc.

Manufactured for:
Aspen Veterinary Resources®, Ltd.
Liberty, MO 64068, USA
www.aspenveterinaryresources.com A279FP 2/22 A280FP 2/22 A281FP 2/22